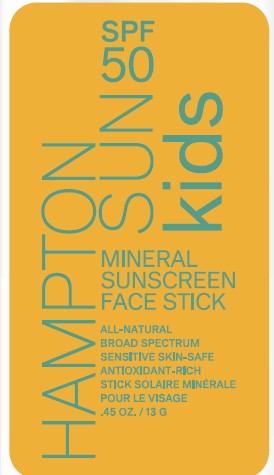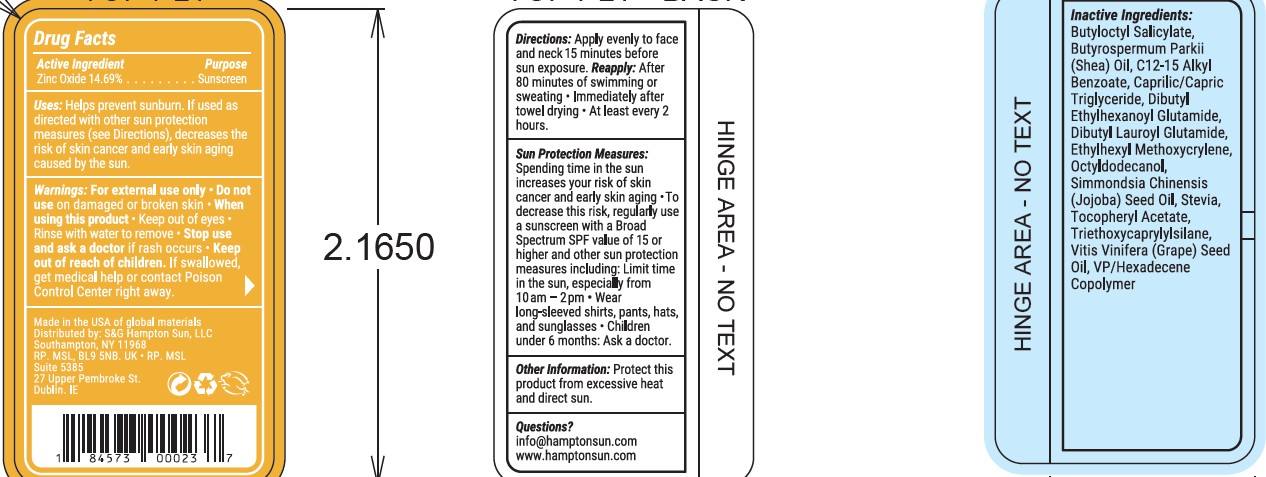 DRUG LABEL: SPF 50 Mineral Sunscreen Kids
NDC: 87170-005 | Form: STICK
Manufacturer: S&C Hampton Sun LLC
Category: otc | Type: HUMAN OTC DRUG LABEL
Date: 20260120

ACTIVE INGREDIENTS: ZINC OXIDE 14.69 g/100 g
INACTIVE INGREDIENTS: BUTYLOCTYL SALICYLATE; BUTYROSPERMUM PARKII (SHEA) BUTTER; C12-15 ALKYL BENZOATE; CAPRYLIC/CAPRIC TRIGLYCERIDE; DIBUTYL ETHYLHEXANOYL GLUTAMIDE; ETHYLHEXYL METHOXYCRYLENE; FRAGRANCE LAVENDER ORC1800979; OCTYLDODECANOL; REBAUDIOSIDE A; SIMMONDSIA CHINENSIS (JOJOBA) SEED OIL; SODIUM HYALURONATE; .ALPHA.-TOCOPHEROL ACETATE; TRIETHOXYCAPRYLYLSILANE; VITIS VINIFERA (GRAPE) SEED OIL; VP/HEXADECENE COPOLYMER

Hampton Sun SPF50 Kids Face Stick

Active Ingredients Purpose

Zinc Oxide 14.69% Sunscreen

Uses

Uses ■ helps prevent sunburn ■ if used as directed with other sun
protection measures (see Directions), decreases the risk of skin
cancer and early skin aging caused by the sun.

Directions

apply liberally to cool, dry skin
15 minutes before sun exposure • reapply:
• after 80 minutes of swimming or sweating
• immediately after towel drying • at least every 2
hours • Sun Protection Measures. Spending time
in the sun increases your risk of skin cancer and
early skin aging. To decrease this risk, regularly
use a sunscreen with a broad spectrum SPF of 15
or higher and other sun protection measures
including: • limit time in the sun,especially from
10 a.m. - 2. p.m. • wear a long-sleeve shirts,
pants, hats, and sunglasses. • children under 6
months: Ask a doctor.

Warnings

For external use only.
Flammable:Do not use white smoking or near heat or flame.
Do not useon damaged or broken skin.
When using this product■ keep out of eyes. Rinse eyes with water
to remove.
Stop use and ask a doctor ifrash occurs.

Keep out of reach children

if swallowed, get medical
help or contact a Polson Control Center right away.

Inactive Ingredients

Butyloctyl Salicylate
Butyrospermum Parkii (Shea) Oil
C12-15 Alkyl Benzoate
Caprylic/Capric Triglyceride
Dibutyl Ethylhexanoyl Glutamide
Dibutyl Lauroyl Glutamide
Ethylhexyl Methoxycrylene
Fragrance
Octyldodecanol
Rebaudioside A
Simmondsia Chinensis (Jojoba) Seed Oil
Sodium Hyaluronate
Tocopheryl Acetate
Triethoxycaprylylsilane
Vitis Vinifera (Grape) Seed Oil
VP/Hexadecene Copolymer